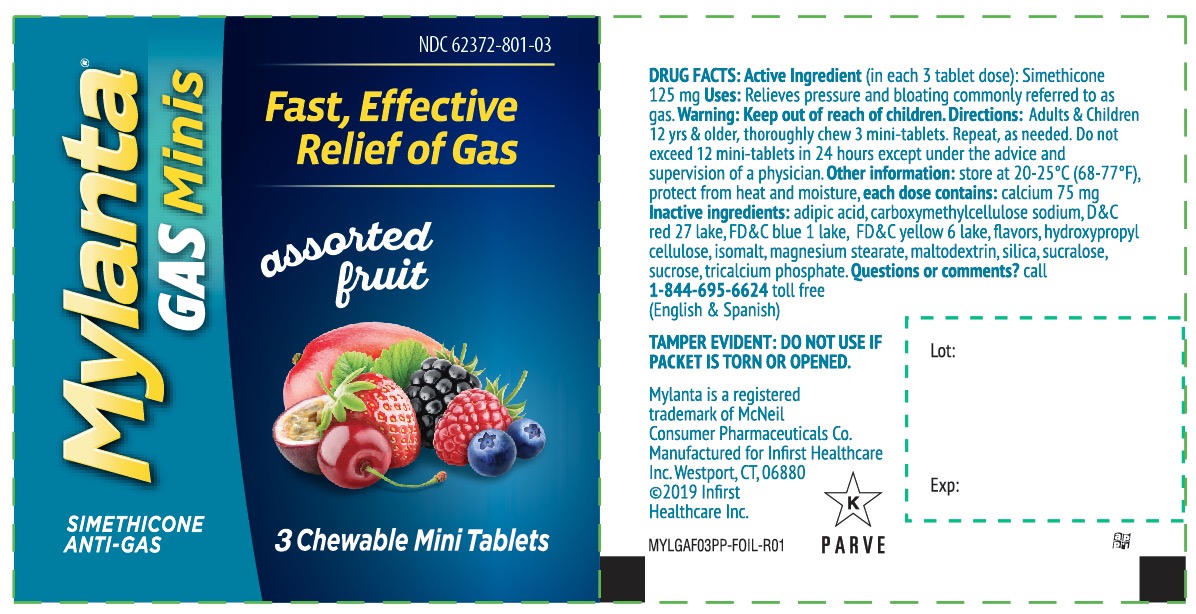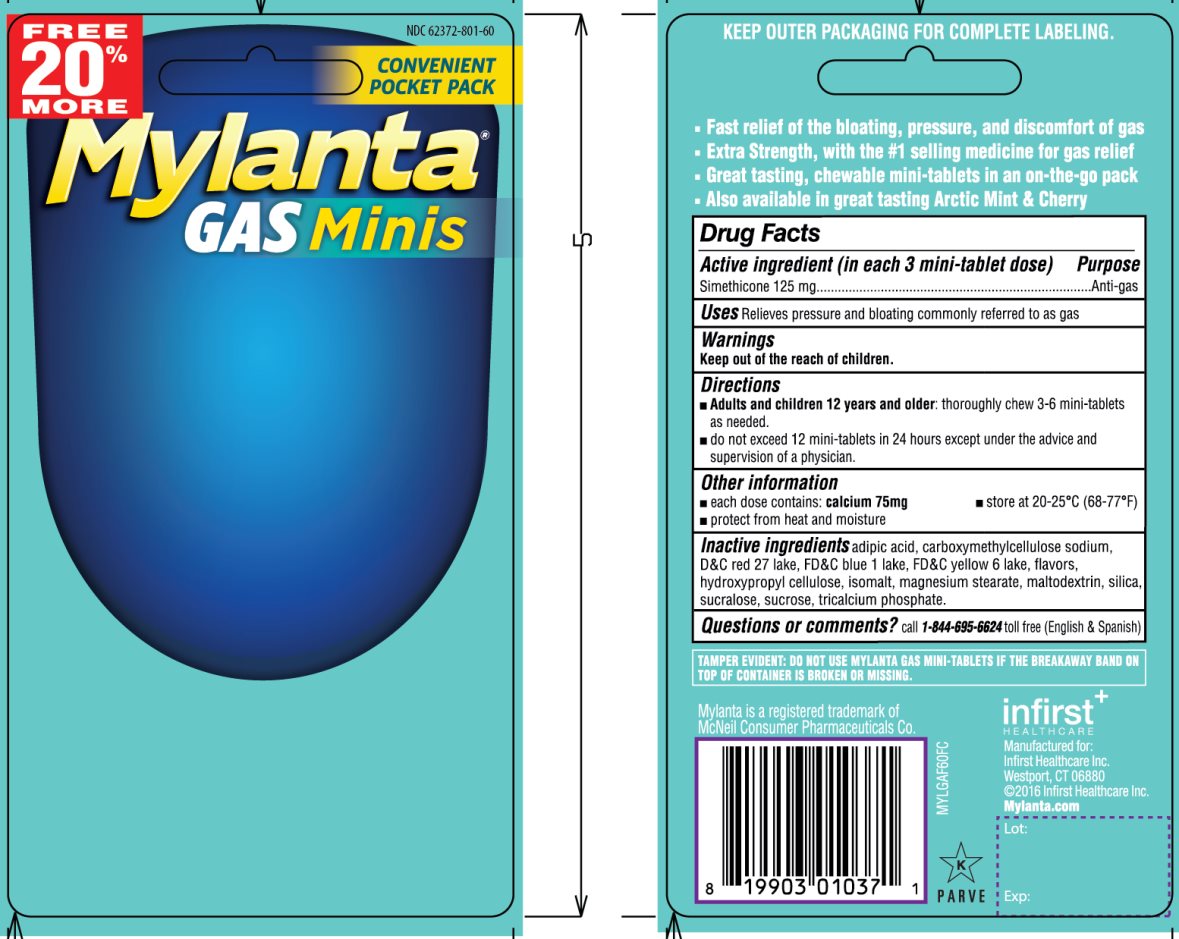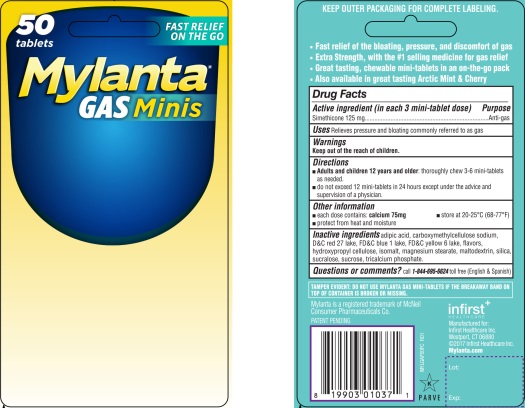 DRUG LABEL: Mylanta Gas Minis Assorted Fruit Flavor
NDC: 62372-801 | Form: TABLET, CHEWABLE
Manufacturer: Infirst Healthcare Inc.
Category: otc | Type: HUMAN OTC DRUG LABEL
Date: 20231204

ACTIVE INGREDIENTS: DIMETHICONE 125 mg/1 1
INACTIVE INGREDIENTS: ADIPIC ACID; CARBOXYMETHYLCELLULOSE SODIUM, UNSPECIFIED FORM; D&C RED NO. 27; FD&C BLUE NO. 1; FD&C YELLOW NO. 6; HYDROXYPROPYL CELLULOSE (1600000 WAMW); ISOMALT; MAGNESIUM STEARATE; MALTODEXTRIN; SILICON DIOXIDE; SUCRALOSE; SUCROSE; TRICALCIUM PHOSPHATE

Mylanta Gas Minis Chewable Tablets

Active ingredient (in each 3 tablet dose)

Simethicone 125 mg

Purpose

Anti-gas

Uses

Relieves pressure and bloating commonly referred to as gas

Warnings

Keep out of the reach of children.

Directions

- Adults and children 12 years and older: thoroughly chew 3-6 mini-tablets as needed.
  • do not exceed 12 mini-tablets in 24 hours except under the advice and supervision of a physician.

Other information

- each dose contains: calcium 75 mg
  • protect from heat and moisture
  • store at 20-25° C (68-77° F)

Inactive ingredients

adipic acid , carboxymethylcellulose sodium ,D&C red 27 lake, FD&C blue 1 lake, FD &C yellow 6 lake, flavors, hydroxypropyl cellulose, isomalt, magnesium stearate, maltodextrin, silica, sucralose, sucrose, tricalcium phosphate,

Questions or comments?

call 1-844-695-6624toll free (English & Spanish)

Principal Display Panel

FREE 20% MORE

CONVENIENT POCKET PACK

Mylanta®

GAS Minis

- Fast relief of the bloating , pressure, and discomfort of gas
- Extra Strength, with the #1 selling medicine for gas relief
- Great tasting ,chewable mini-tablets in an on-the-go pack
- Also available in great tasting Arctic Mint & Cherry

TAMPER EVIDENT: DO NOT USE MYLANTA GAS MINI-TABLETS IF THE BREAKAWAY BAND ON TOP OF CONTAINER IS BROKEN OR MISSING.

1. Mylanta is a registered trademark of McNeil Consumer Pharmaceuticals Co.

Patent pending

infirst^+

HEALTHCARE

Manufactured for:

Infirst Healthcare Inc.

Westport, CT 06880

©2016 Infirst Healthcare Inc.

Mylanta.com

KEEP OUTER PACKAGING FOR COMPLETE LABELING